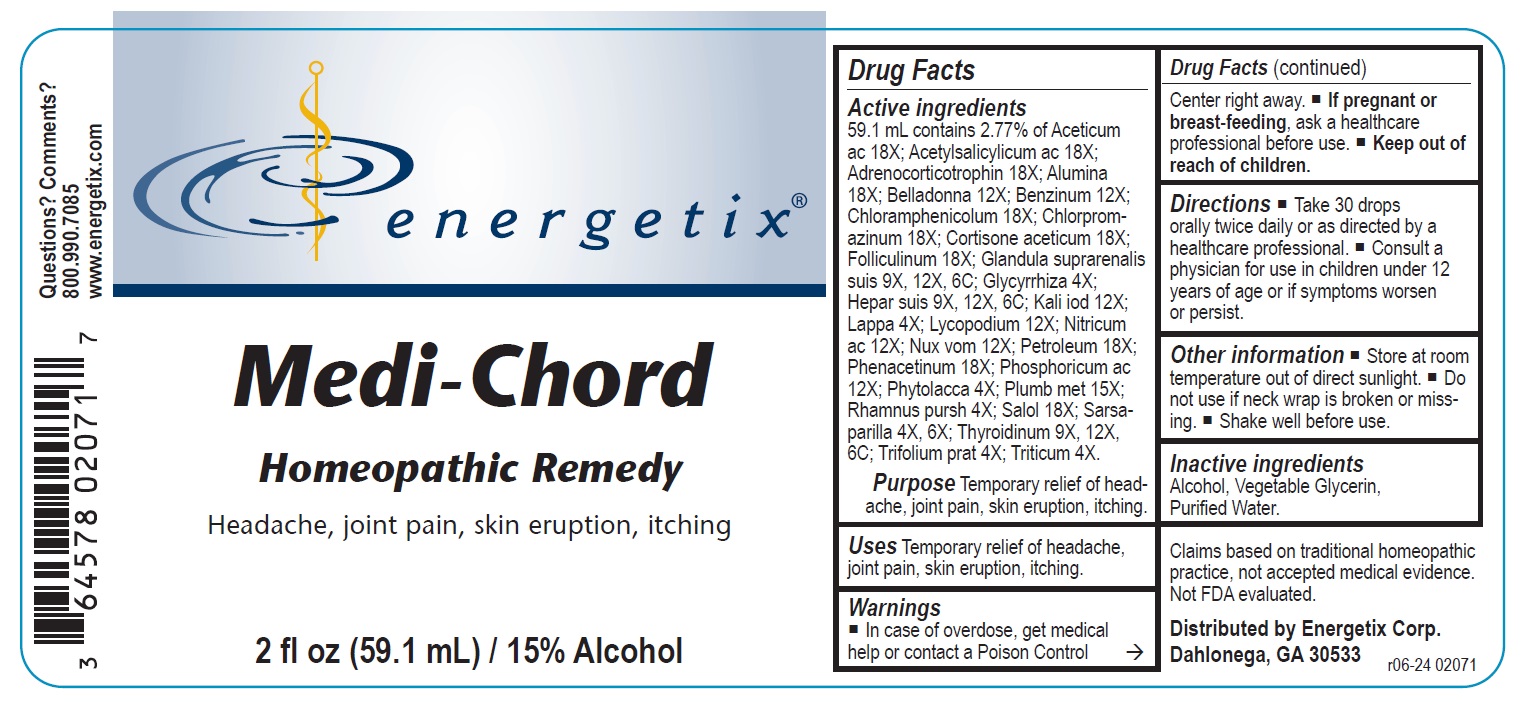 DRUG LABEL: Medi-Chord
NDC: 64578-0060 | Form: LIQUID
Manufacturer: Energetix Corporation
Category: homeopathic | Type: HUMAN OTC DRUG LABEL
Date: 20241120

ACTIVE INGREDIENTS: ACETIC ACID 18 [hp_X]/59.1 mL; ASPIRIN 18 [hp_X]/59.1 mL; CORTICOTROPIN HUMAN 18 [hp_X]/59.1 mL; ALUMINUM 18 [hp_X]/59.1 mL; ATROPA BELLADONNA 12 [hp_X]/59.1 mL; BENZENE 12 [hp_X]/59.1 mL; CHLORAMPHENICOL 18 [hp_X]/59.1 mL; CHLORPROMAZINE 18 [hp_X]/59.1 mL; CORTISONE ACETATE 18 [hp_X]/59.1 mL; ESTRONE 18 [hp_X]/59.1 mL; SUS SCROFA ADRENAL GLAND 9 [hp_X]/59.1 mL; GLYCYRRHIZA GLABRA 4 [hp_X]/59.1 mL; PORK LIVER 9 [hp_X]/59.1 mL; POTASSIUM IODIDE 12 [hp_X]/59.1 mL; ARCTIUM LAPPA ROOT 4 [hp_X]/59.1 mL; LYCOPODIUM CLAVATUM SPORE 12 [hp_X]/59.1 mL; NITRIC ACID 12 [hp_X]/59.1 mL; STRYCHNOS NUX-VOMICA SEED 12 [hp_X]/59.1 mL; KEROSENE 18 [hp_X]/59.1 mL; PHENACETIN 18 [hp_X]/59.1 mL; PHOSPHORIC ACID 12 [hp_X]/59.1 mL; PHYTOLACCA AMERICANA ROOT 4 [hp_X]/59.1 mL; LEAD 15 [hp_X]/59.1 mL; FRANGULA PURSHIANA BARK 4 [hp_X]/59.1 mL; PHENYL SALICYLATE 18 [hp_X]/59.1 mL; SARSAPARILLA 4 [hp_X]/59.1 mL; THYROID, UNSPECIFIED 9 [hp_X]/59.1 mL; TRIFOLIUM PRATENSE FLOWER 4 [hp_X]/59.1 mL; ELYMUS REPENS ROOT 4 [hp_X]/59.1 mL
INACTIVE INGREDIENTS: WATER; ALCOHOL; GLYCERIN

Medi-Chord

ACTIVE INGREDIENT

Active ingredients59.1 mL contains 2.77% of Aceticum ac 18X; Acetylsalicylicum ac 18X; Adrenocorticotrophin 18X; Alumina 18X; Belladonna 12X; Benzinum 12X; Chloramphenicolum 18X; Chlorpromazinum 18X; Cortisone aceticum 18X; Folliculinum 18X; Glandula suprarenalis suis 9X, 12X, 6C; Glycyrrhiza 4X; Hepar suis 9X, 12X, 6C; Kali iod 12X; Lappa 4X; Lycopodium 12X; Nitricum ac 12X; Nux vom 12X; Petroleum 18X; Phenacetinum 18X; Phosphoricum ac 12X; Phytolacca 4X; Plumb met 15X; Rhamnus pursh 4X; Salol 18X; Sarsaparilla 4X, 6X; Thyroidinum 9X, 12X, 6C; Trifolium prat 4X; Triticum 4X.

Claims based on traditional homeopathic practice, not accepted medical evidence. Not FDA evaluated.

Uses

Temporary relief of headache, joint pain, skin eruption, itching.

Warnings

- In case of overdose, get medical help or contact a Poison Control Center right away.
- If pregnant or breast-feeding, ask a healthcare professional before use.

- Keep out of reach of children.

Directions

- Take 30 drops orally twice daily or as directed by a healthcare professional.
- Consult a physician for use in children under 12 years of age or if symptoms worsen or persist.

Other information

- Store at room temperature out of direct sunlight.
- Do not use if neck wrap is broken or missing.
- Shake well before use.

Inactive ingredients

Alcohol, Vegetable Glycerin, Purified Water.

QUESTIONS

Distributed by Energetix Corp.

Dahlonega, GA 30533

Questions? Comments?

800.990.7085

www.energetix.com

PACKAGE LABEL

energetix

Medi-Chord

Homeopathic Remedy

Headache, joint pain, skin eruption, itching

2 fl oz (59.1 mL) / 15% Alcohol

PURPOSE

Purpose Temporary relief of headache, joint pain, skin eruption, itching.